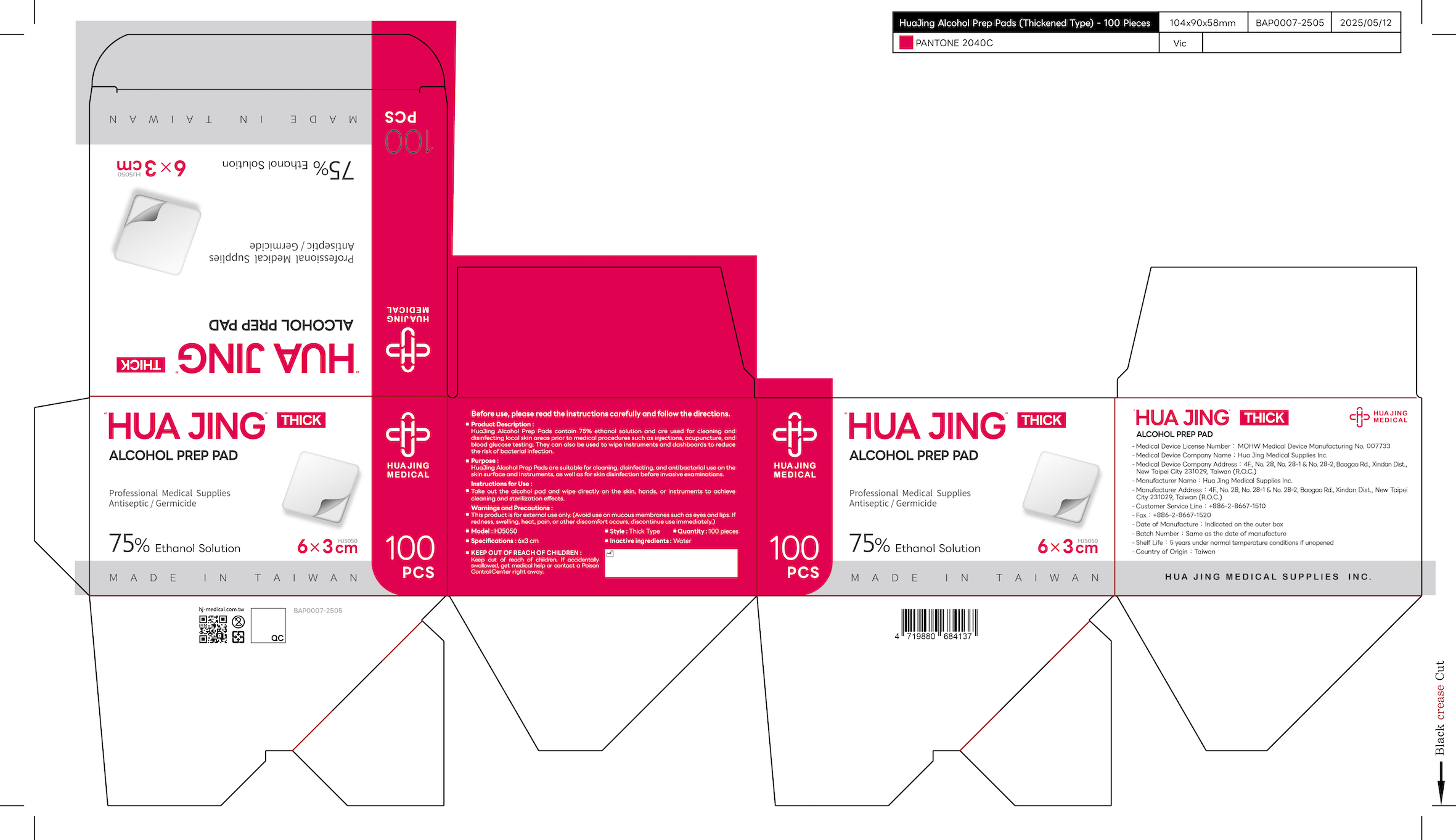 DRUG LABEL: Hua Jing Alcohol Prep Pad (Thick)
NDC: 83170-002 | Form: CLOTH
Manufacturer: Hua Jing Medical Supplies INC.
Category: otc | Type: HUMAN OTC DRUG LABEL
Date: 20260210

ACTIVE INGREDIENTS: ALCOHOL 0.75 mL/1 mL
INACTIVE INGREDIENTS: WATER

83170-002-02, Hua Jing Alcohol Prep Pad (Thick)

Hua Jing Alcohol Prep Pad (Thick), Package NDC: 83170-002-01

Hua Jing Alcohol Prep Pad (Thick)

Active Ingredient(s): 75% Ethanol Solution

Purpose

HuaJing Alcohol Prep Pads are suitable for cleaning, disinfecting, and antibacterial use on the skin surface and instruments, as well as for skin disinfection before invasive examinations.

Use

Instructions for Use:

Take out the alcohol pad and wipe directly on the skin, hands, or instruments to achieve cleaning and sterilization effects.

Warnings

Warnings and Precautions:

This product is for external use only. (Avoid use on mucous membranes such as eyes and lips. If redness, swelling, heat, pain, or other discomfort occurs, discontinue use immediately.)

Keep out of reach of children. If accidentally swallowed, get medical help or contact a Poison Control Center right away.

Inactive ingredients

Inactive ingredients: Water

Product Description

HuaJing Alcohol Prep Pads contain 75% ethanol solution and are used for cleaning and disinfecting local skin areas prior to medical procedures such as injections, acupuncture, and blood glucose testing. They can also be used to wipe instruments and dashboards to reduce the risk of bacterial infection.

Model: HJ5050

Style: Thick Type

Specifications: 6x3 cm

Quantity: 100 pieces

Hua Jing Alcohol Prep Pad, Package NDC: 83170-002-01

Hua Jing Alcohol Prep Pad (Thick), Package NDC: 83170-002-01